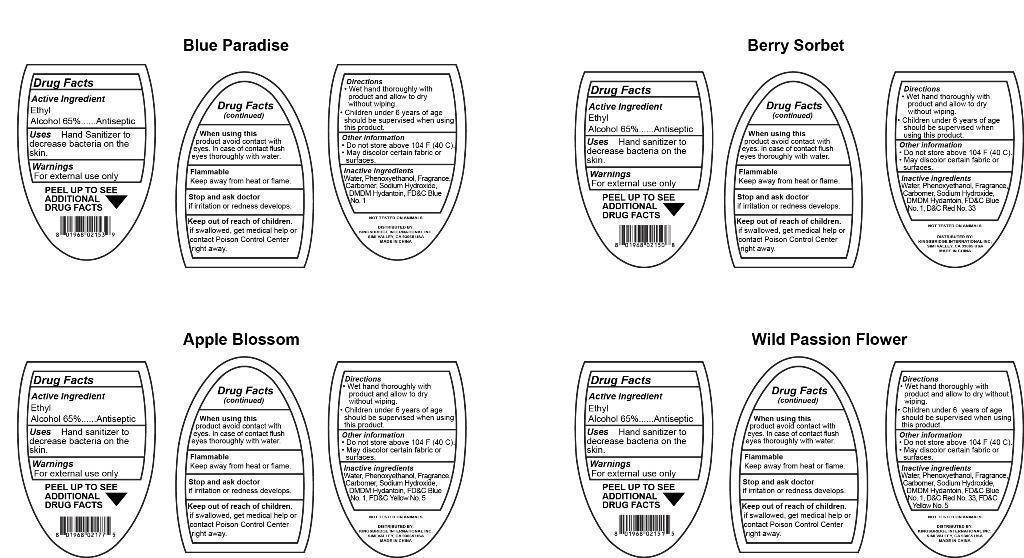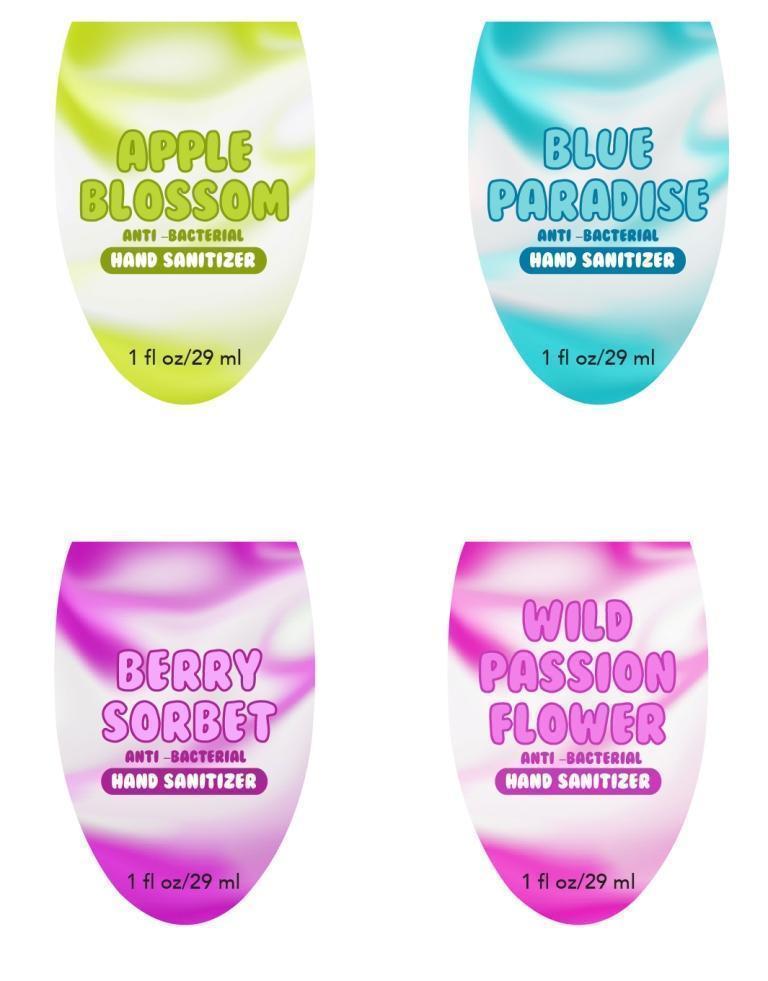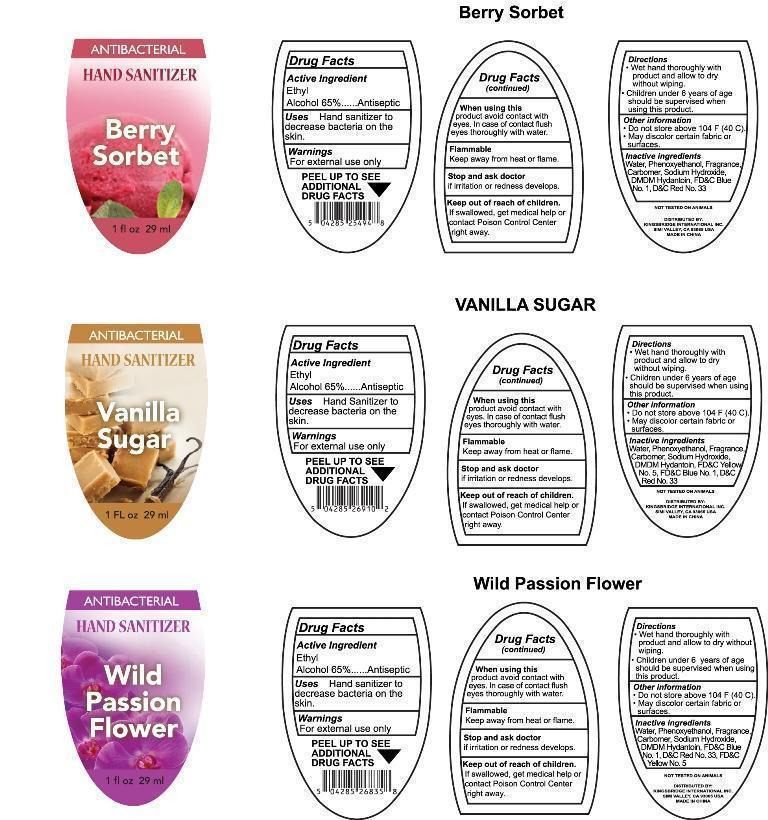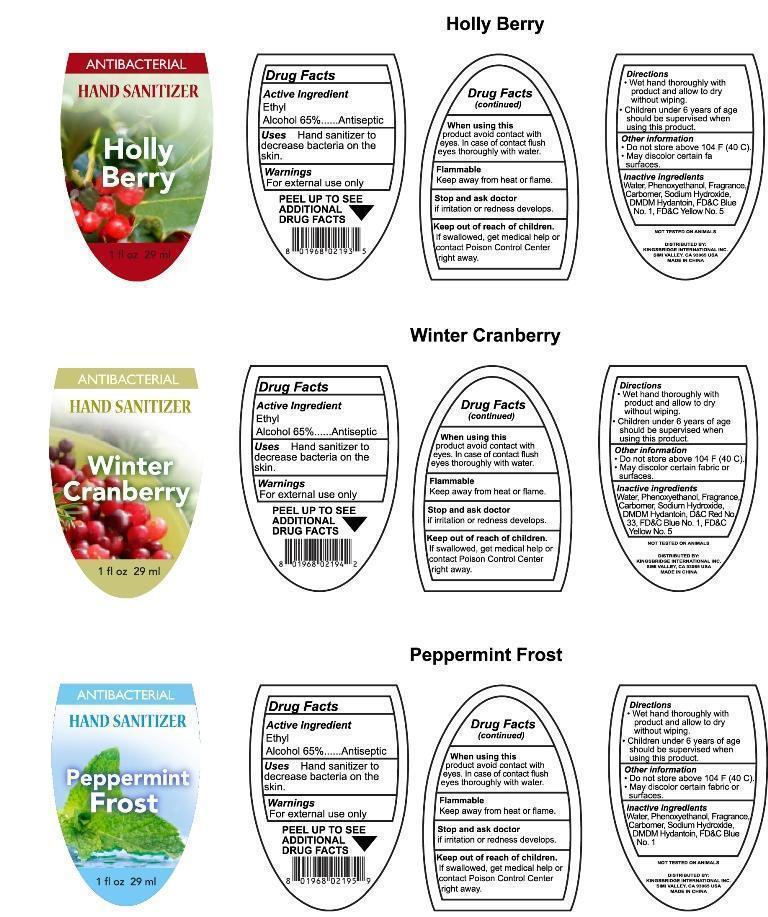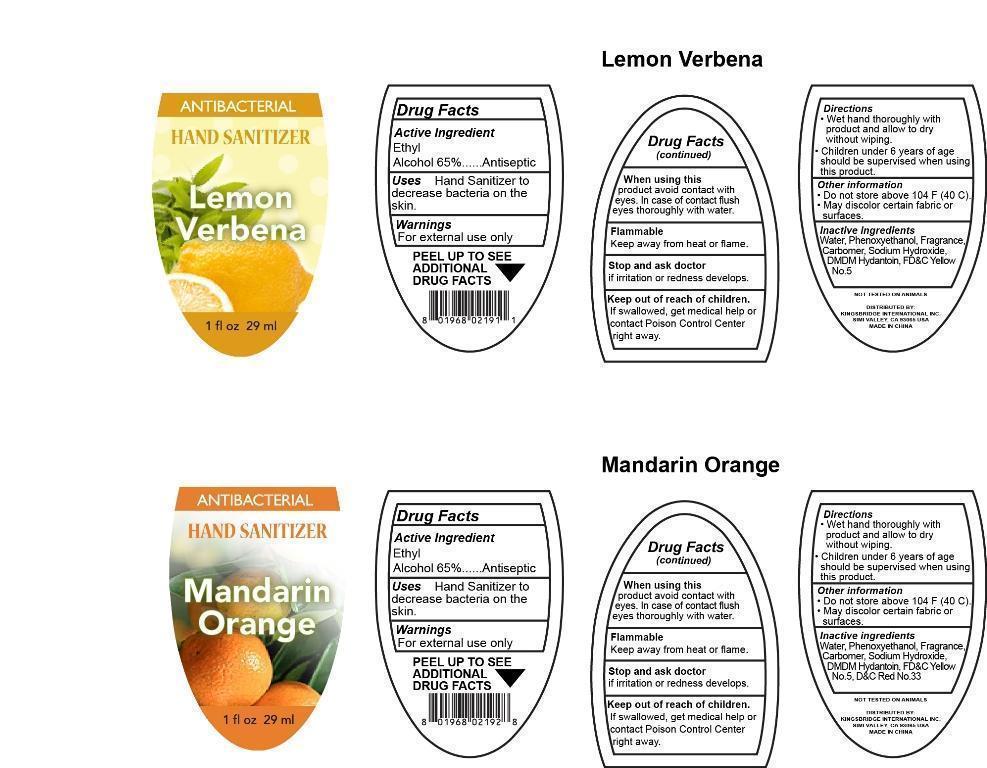 DRUG LABEL: HAND SANITIZER 
NDC: 51706-600 | Form: GEL
Manufacturer: Landy International
Category: otc | Type: HUMAN OTC DRUG LABEL
Date: 20150421

ACTIVE INGREDIENTS: ALCOHOL 65 mL/100 mL
INACTIVE INGREDIENTS: WATER; PHENOXYETHANOL; CARBOMER COPOLYMER TYPE A; SODIUM HYDRIDE; DMDM HYDANTOIN; FD&C BLUE NO. 1; FD&C YELLOW NO. 5

Drug Fact

Active Ingredient

Ethyl Alcohol 65%

Purpose

Antiseptic

Uses

To decrease bacteria on the skin.

Warning

For external use only.
When using this product avoid contact with eyes.In case of contact flush eyes thoroughly with water.

Flammable.
Keep away from heat and flame.
Stop use and consult a doctor
if irritation and redness develop and persist for more than 72 hours.

Keep out of reach of children.

If swallowed,get medical help or contact Poison Control Center right away

Directions

■ Wet hands with product and allow to dry without wiping.

Children under 6 years of age should be supervised when using this product.

Other Information

do not store above 104F (40C)
may discolor certain fa surfaces.

Inactive Ingredient

WATER,PHENOXYETHANOL,CARBOMER COPOLYMER TYPE A,SODIUM HYDRIDE,DMDM HYDANTOIN ,FD&C BLUE NO. 1,FD&C YELLOW NO. 5